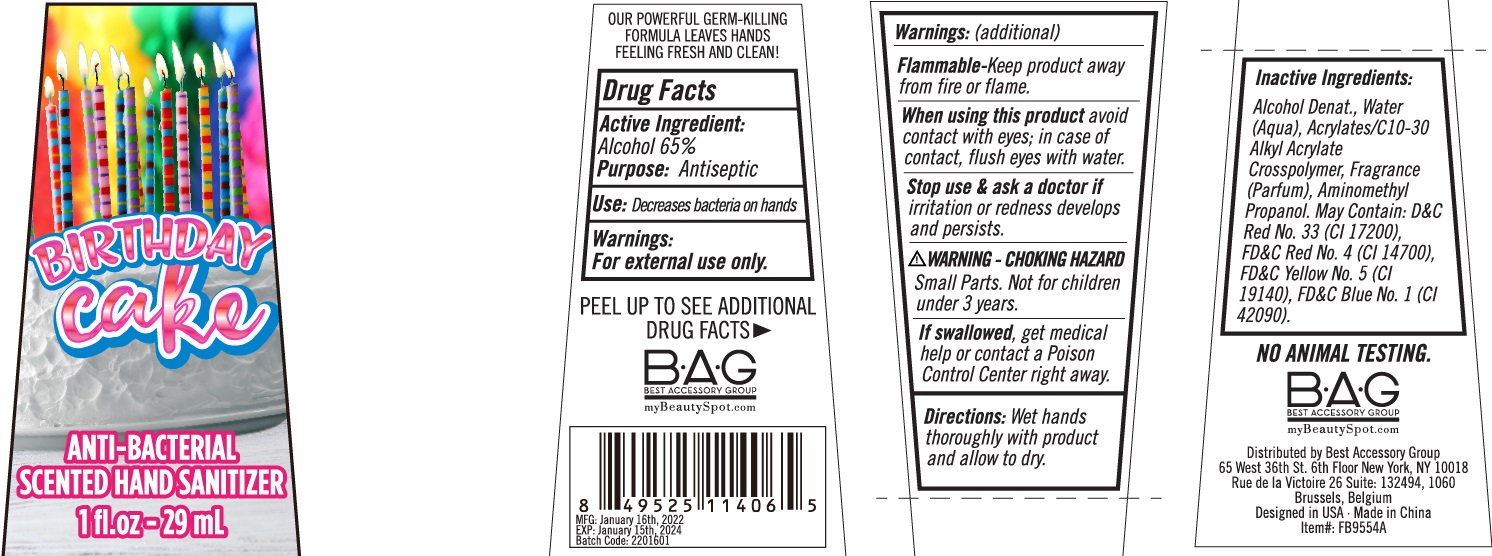 DRUG LABEL: Birthday Cake Anti-Bacterial Scented Hand Sanitizer
NDC: 56136-163 | Form: GEL
Manufacturer: Ganzhou Olivee Cosmetic Co., Ltd.
Category: otc | Type: HUMAN OTC DRUG LABEL
Date: 20220121

ACTIVE INGREDIENTS: ALCOHOL 65 mL/100 mL
INACTIVE INGREDIENTS: water; CARBOMER COPOLYMER TYPE A; AMINOMETHYLPROPANOL

hand sanitizer

Active ingredient

Alcohol 65%

Purpose

Antiseptic

USE

Decrease bacteria on hands

Warnings

For external only.

Flammable-keep product awau from fire or flame.

Waring - Choking Hazard

Small parts. Not for children under 3 years.

When using this product

avoid contact with eyes; in case of contact, flush eyes with water.

Stop use and ask a doctor if

- irritation and redness develops and persists.

Keep out of reach of children.

If swallowed, get medical help or contact a Poison Control Center right away.

Directions

Wet hands thoroughly with product and allow to dry.

Inactive ingredients

Alcool Denat., Water (Aqua), Acrylates/c 10-30 Alkyl Acrylate Crosspolymer, Aminomethyl Propanol, Fragrace (Parfum). May contain: FD&C No. 4 (C.l. 14700), D&C Red No. 33 (Cl 17200), FD&C Yellow 5, FD&C Blue No. 1 (Cl 42090).